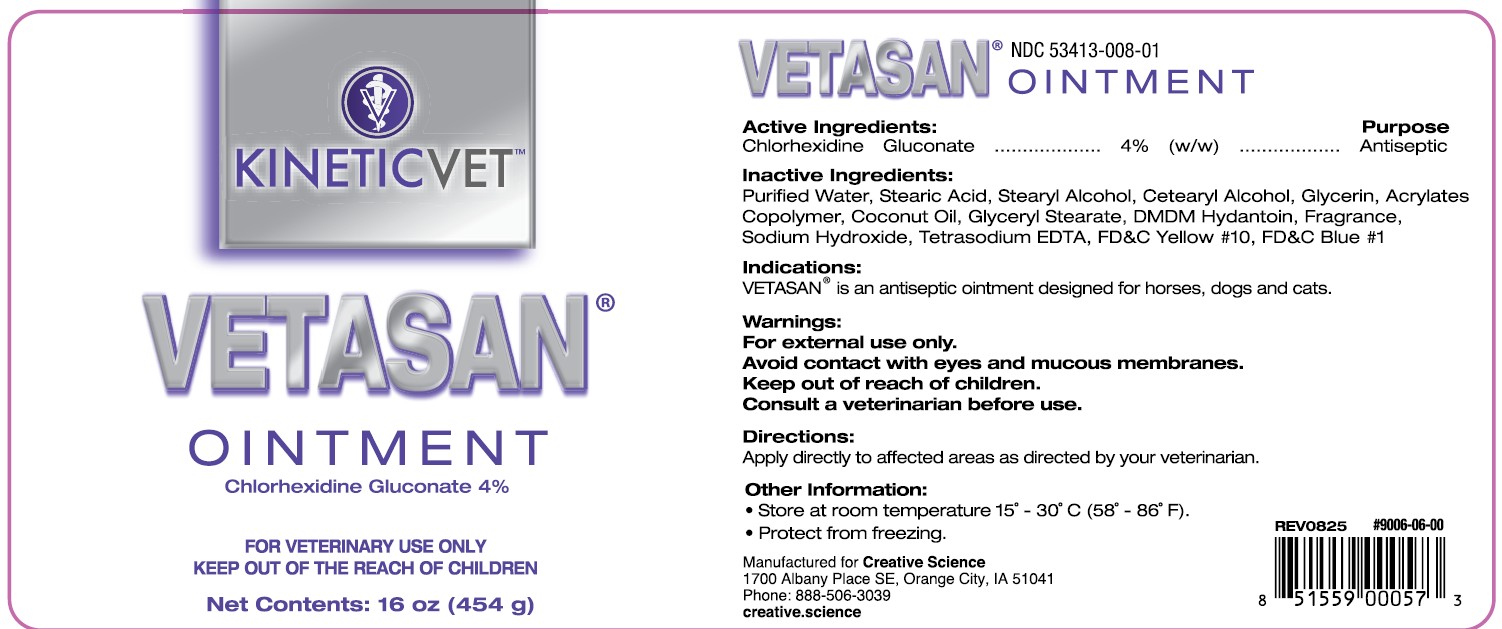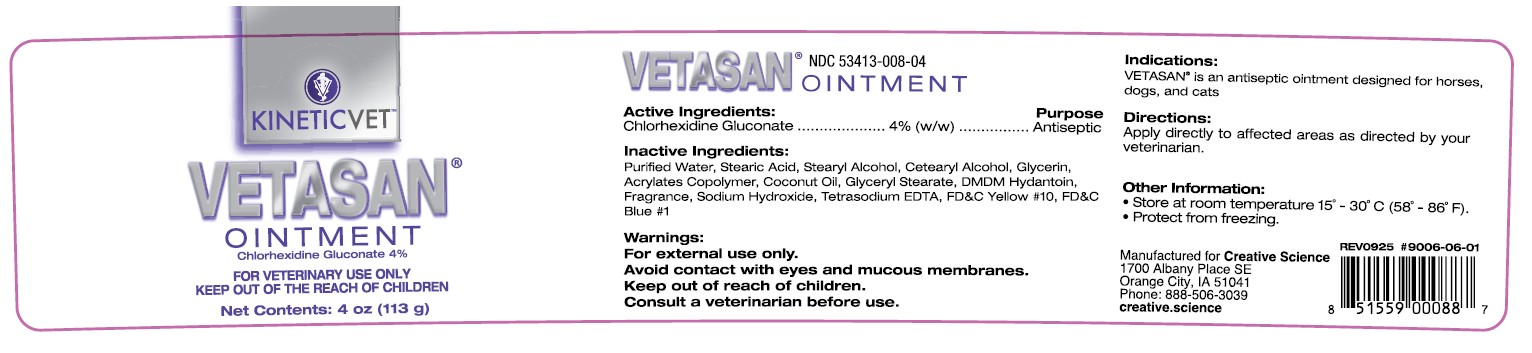 DRUG LABEL: Vetasan
NDC: 53413-008 | Form: CREAM
Manufacturer: Creative Science
Category: animal | Type: OTC ANIMAL DRUG LABEL
Date: 20251206

ACTIVE INGREDIENTS: CHLORHEXIDINE GLUCONATE 4 g/100 g

Vetasan Ointment

NDC 53413-008-04
NDC 53413-008-01

Active Ingredients: Purpose

Chlorhexidine Gluconate.........4% (w/w) ................ Antiseptic

Inactive Ingredients:

Purified Water, Stearic Acid, Stearyl Alcohol, Glycerin, Acrylates Copolymer, Coconut Oil, Glyceryl Stearate, DMDM Hydantoin, Fragrance, Sodium Hydroxide, Tetrasodium EDTA, FD&C Yellow #10, FD&C Blue #1

Indications:

VETASAN® is an antiseptic ointment designed for horses, dogs and cats.

Warnings:

For external use only.

Avoid contact with eyes and mucous membranes.

Keep out of reach of children.

Consult a veterinarian before use.

Directions:

Apply directly to affected areas as directed by your veterinarian.

Other Information:

- Store at room temperature 15° - 30°C (58° - 86°F).
- Protect from freezing.

Rev 0925 UPC 851559000887 - 4 0z

Rev 0825 UPC 851559000573 - 16 oz

Manufactured for Creative Science

1700 Albany Place SE, Orange City, IA 51041

Phone: 888-506-3039

creative.science

KINETICVET™

VETASAN®

OINTMENT

Chlorhexidine Gluconate 4%

FOR VETERINARY USE ONLY

KEEP OUT OF THE REACH OF CHILDREN

Net Contents: 4 oz (454 g)

Net Contents: 16 oz (113 g)

Add image transcription here...

Add image transcription here...